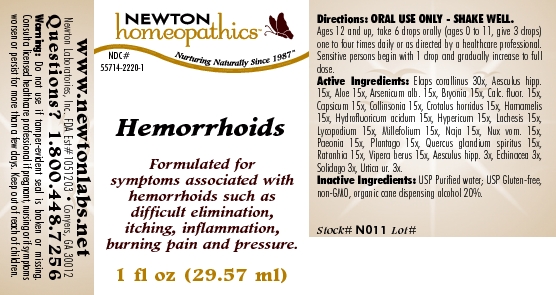 DRUG LABEL: Hemorrhoids 
NDC: 55714-2220 | Form: LIQUID
Manufacturer: Newton Laboratories, Inc.
Category: homeopathic | Type: HUMAN OTC DRUG LABEL
Date: 20110301

ACTIVE INGREDIENTS: Micrurus Corallinus Venom 30 [hp_X]/1 mL; Horse Chestnut 15 [hp_X]/1 mL; Aloe 15 [hp_X]/1 mL; Arsenic Trioxide 15 [hp_X]/1 mL; Bryonia Alba Root 15 [hp_X]/1 mL; Calcium Fluoride 15 [hp_X]/1 mL; Capsicum 15 [hp_X]/1 mL; Collinsonia Canadensis Root 15 [hp_X]/1 mL; Crotalus Horridus Horridus Venom 15 [hp_X]/1 mL; Hamamelis Virginiana Root Bark/stem Bark 15 [hp_X]/1 mL; Hydrofluoric Acid 15 [hp_X]/1 mL; Hypericum Perforatum 15 [hp_X]/1 mL; Lachesis Muta Venom 15 [hp_X]/1 mL; Lycopodium Clavatum Spore 15 [hp_X]/1 mL; Achillea Millefolium 15 [hp_X]/1 mL; Naja Naja Venom 15 [hp_X]/1 mL; Strychnos Nux-vomica Seed 15 [hp_X]/1 mL; Paeonia Officinalis Root 15 [hp_X]/1 mL; Plantago Major 15 [hp_X]/1 mL; Quercus Robur Nut 15 [hp_X]/1 mL; Krameria Lappacea Root 15 [hp_X]/1 mL; Vipera Berus Venom 15 [hp_X]/1 mL; Echinacea, Unspecified 3 [hp_X]/1 mL; Solidago Virgaurea Flowering Top 3 [hp_X]/1 mL; Urtica Urens 3 [hp_X]/1 mL
INACTIVE INGREDIENTS: Alcohol

Hemorrhoids

INDICATIONS & USAGE SECTION

Hemorrhoids Formulated for symptoms associated with hemorrhoids such as difficult elimination, itching, inflammation, burning pain and pressure.

DOSAGE & ADMINISTRATION SECTION

Directions: ORAL USE ONLY - SHAKE WELL. Ages 12 and up, take 6 drops orally (ages 0 to 11, give 3 drops) one to four times daily or as directed by a healthcare professional. Sensitive persons begin with 1 drop and gradually increase to full dose.

OTC - ACTIVE INGREDIENT SECTION

Elaps corallinus 30x, Aesculus hipp.15x, Aloe 15x, Arsenicum alb. 15x, Bryonia 15x, Calc. fluor. 15x, Capsicum 15x, Collinsonia 15x, Crotalus horridus 15x, Hamamelis 15x, Hydrofluoricum acidum 15x, Hypericum 15x, Lachesis 15x, Lycopodium 15x, Millefolium 15x, Naja 15x, Nux vom. 15x, Paeonia 15x, Plantago 15x, Quercus glandium spiritus 15x, Ratanhia 15x, Vipera berus 15x, Aesculus hipp. 3x, Echinacea 3x, Solidago 3x, Urtica ur. 3x.

OTC - PURPOSE SECTION

Formulated for symptoms associated with hemorrhoids such as difficult elimination, itching, inflammation, burning pain and pressure.

INACTIVE INGREDIENT SECTION

Inactive Ingredients: USP Purified Water; USP Gluten-free, non-GMO, organic cane dispensing alcohol 20%

QUESTIONS SECTION

www.newtonlabs.net Newton Laboratories, Inc. FDA Est # 1051203 - Conyers, GA 30012
Questions? 1.800.448.7256

WARNINGS SECTION

Warning: Do not use if tamper - evident seal is broken or missing. Consult a licensed healthcare professional if pregnant, nursing or if symptoms worsen or persist for more than a few days. Keep out of reach of children

OTC - PREGNANCY OR BREAST FEEDING SECTION

Consult a licensed healthcare professional if pregnant, nursing or if symptoms worsen or persist for more than a few days.

OTC - KEEP OUT OF REACH OF CHILDREN SECTION

Keep out of reach of children